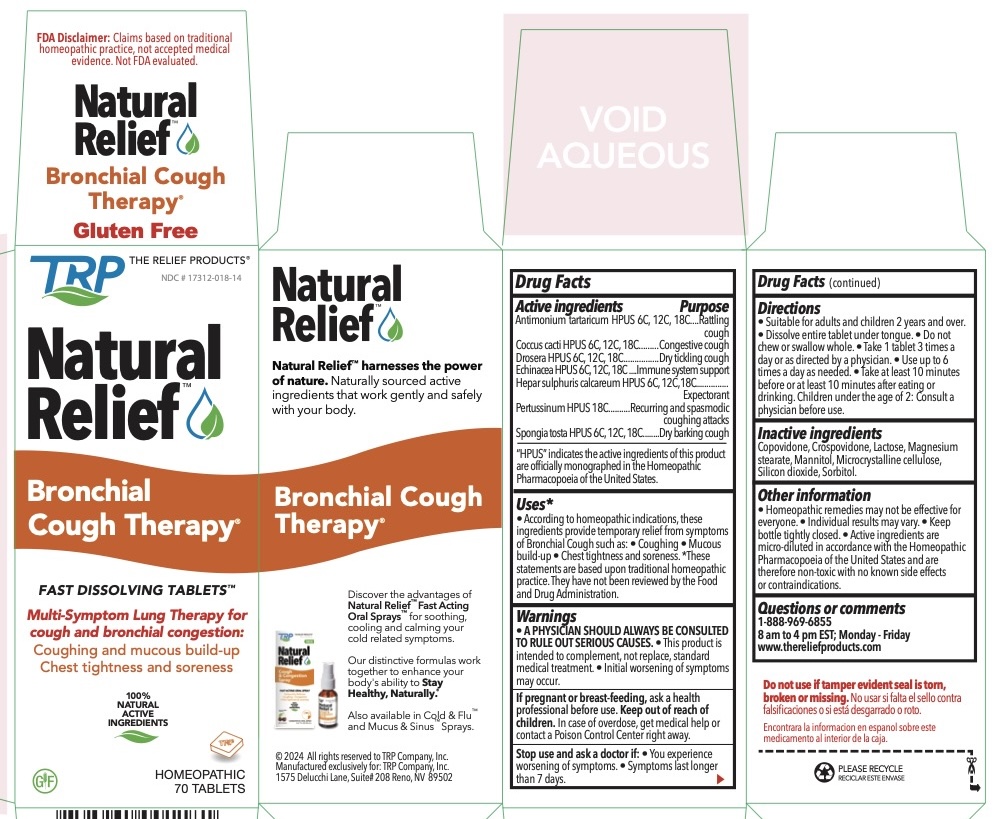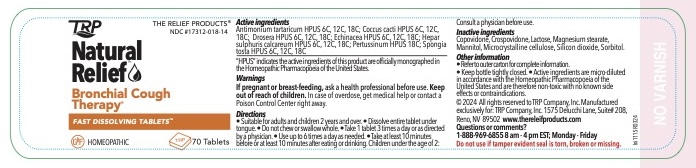 DRUG LABEL: Bronchial Cough Therapy
NDC: 17312-018 | Form: TABLET, ORALLY DISINTEGRATING
Manufacturer: TRP Company
Category: homeopathic | Type: HUMAN OTC DRUG LABEL
Date: 20251215

ACTIVE INGREDIENTS: SPONGIA OFFICINALIS SKELETON, ROASTED 6 [hp_C]/1 1; ANTIMONY POTASSIUM TARTRATE 6 [hp_C]/1 1; PROTORTONIA CACTI 6 [hp_C]/1 1; DROSERA ROTUNDIFOLIA 6 [hp_C]/1 1; ECHINACEA, UNSPECIFIED 6 [hp_C]/1 1; CALCIUM SULFIDE 6 [hp_C]/1 1; HUMAN SPUTUM, BORDETELLA PERTUSSIS INFECTED 18 [hp_C]/1 1
INACTIVE INGREDIENTS: MANNITOL; SORBITOL; CROSPOVIDONE; CELLULOSE, MICROCRYSTALLINE; COPOVIDONE; SILICON DIOXIDE; LACTOSE; MAGNESIUM STEARATE

Bronchial Cough Therapy

Active Ingredients |  | Purpose
Antimonium tartaricum HPUS | 6c, 12c, 18c | Rattling cough
Coccus cacti HPUS | 6c, 12c, 18c | Congestive cough
Drosera HPUS | 6c, 12c, 18c | Dry tickling cough
Echinacea HPUS | 6c, 12c, 18c | Immune system support
Hepar sulphuris calcareum HPUS | 6c, 12c, 18c | Expectorant
Pertussinum HPUS | 18c | Recurring and Spasmodic coughing attacks
Spongia tosta HPUS | 6c, 12c, 18c | Dry barking cough

The letters HPUS indicate that the components of this product are officially monographed in the Homeopathic Pharmacopoeia of the United States.

Uses

According to homeopathic indications these ingredients provide temporary relief of symptoms of Bronchial Cough such as: • coughing • mucous build-up • chest tightness and • chest soreness after diagnosis by a physician.

Warnings

USE ONLY AFTER DIAGNOSIS BY A PHYSICIAN.

- This product is a not a fast acting (rescue) inhaler.
- This product is intended to complement, not replace, standard medical treatment.
- Initial worsening of symptoms may occur.
- A physician should always be consulted to rule out serious causes.
- In case of overdose, get medical help or contact a Poison Control Center right away.

Stop use and ask a doctor if:

- You experience worsening symptoms.
- If symptoms last longer than 7 days.

PREGNANCY OR BREAST FEEDING

If pregnant or breast-feeding, ask a health professional before use.

Directions

- Suitable for adults and children 12 years and above.
- Dissolve entire tablet under tongue.
- Do not chew or swallow whole.
- Take 1 tablet 3 times a day or as directed by a physician.
- Use up to 6 times a day as needed.
- Take at least 10 minutes before or at least 10 minutes after eating or drinking.
- Children under the age of 12: consult a physician before use.

Other information

- Active ingredients are micro-diluted in accordance with the Homeopathic Pharmacopoeia of the United States and are therefore non-toxic with no known side effects.
- Store in a cool dark location.

Inactive Ingredients

Advantol® 300, Lactose, Magnesium Stearate, Mannitol, Microcrystalline Cellulose.

QUESTIONS

For more information and to order related products call toll free: 888-969-6855 or trpcompany.com

Principal Display Panel

FDA Disclaimer: Claims based on traditional
homeopathic practice, not accepted medical
evidence. Not FDA evaluated.